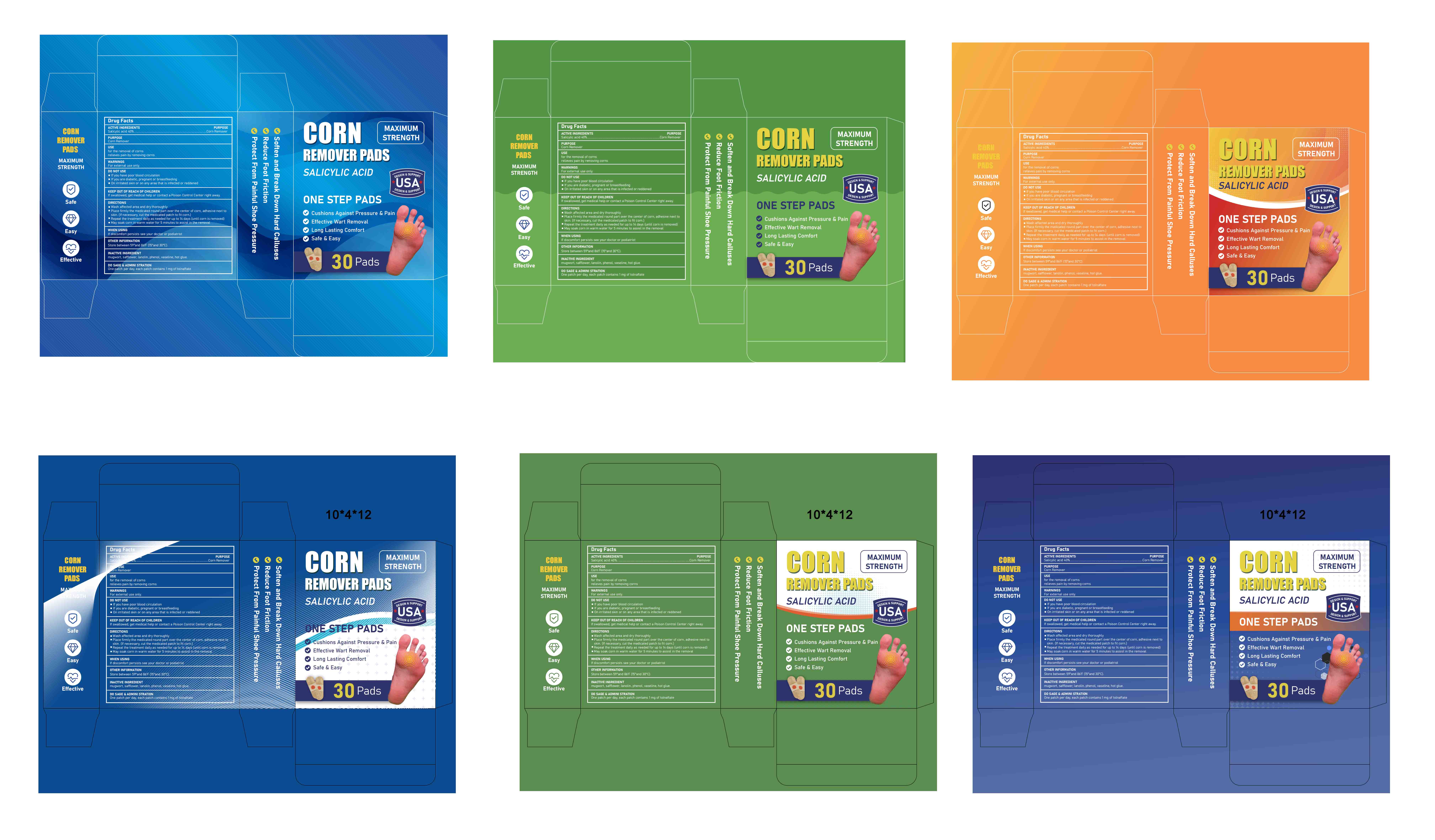 DRUG LABEL: CORN REMOVER PADS
NDC: 85839-004 | Form: PATCH
Manufacturer: Shenzhen Finona Information Technology Co., Ltd
Category: otc | Type: HUMAN OTC DRUG LABEL
Date: 20250626

ACTIVE INGREDIENTS: SALICYLIC ACID 0.4 g/1 1
INACTIVE INGREDIENTS: ARTEMISIA VULGARIS WHOLE; PHENOL; WHITE PETROLATUM; SAFFLOWER; LANOLIN

85839-004 CORN REMOVER PADS

ACTIVE INGREDIENT

Salicylic acid 40%

PURPOSE

Corn Remover

INDICATIONS AND USAGE

for the removal of corns relieves pain by removing corns

WARNINGS

For external use only.

DO NOT USE

If your have poor blood cireulation
lf you are dlabetic, pregnant or breastfeeding
On irritated skin or on any area that is infected or reddened

WHEN USING

If discomfort persists see your doctor or podiatrist

KEEP OUT OF REACH OF CHILDREN

If swallowed, get medical help or contact a Poison Control Center right away.

DOSAGE AND ADMINISTRATION

Wash affected area and dry thoroughily
Place firmly the medicated round part over the center of corn, adhesive next to skin.(if necessary, cut the medicated patch to fit cor.)
Repeat the treatment dally as needed forup to 14 days (untll corn is removed)
May soak corn in warm water for 5 minutes to assist in the removal

INACTIVE INGREDIENT

mugwort
safflower
lanolin
phenol
vaseline
hot glue